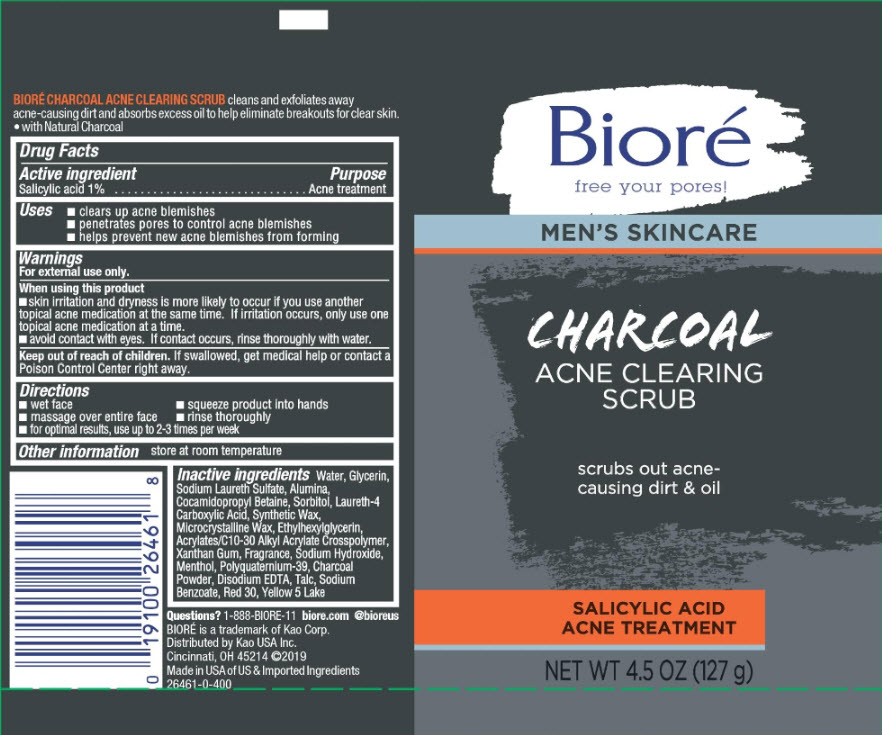 DRUG LABEL: Biore
NDC: 10596-192 | Form: GEL
Manufacturer: Kao USA Inc.
Category: otc | Type: HUMAN OTC DRUG LABEL
Date: 20190929

ACTIVE INGREDIENTS: SALICYLIC ACID 1 g/100 g
INACTIVE INGREDIENTS: CARBOMER COPOLYMER TYPE A; SODIUM LAURETH SULFATE; ALUMINUM; POLYQUATERNIUM-39 (22.5/51/26.5 ACRYLIC ACID/ACRYLAMIDE/DADMAC; 1600000 MW); WATER; GLYCERIN; MICROCRYSTALLINE WAX; SODIUM HYDROXIDE; XANTHAN GUM; MENTHOL; D&C RED NO. 30; SODIUM BENZOATE; FD&C YELLOW NO. 5; TALC; COCAMIDOPROPYL BETAINE; SORBITOL; ETHYLHEXYLGLYCERIN; ACTIVATED CHARCOAL; EDETATE DISODIUM; SYNTHETIC WAX (1200 MW); LAURETH-4 CARBOXYLIC ACID

Biore Men's Skincare Charcoal Acne Clearing Scrub

BIORE CHARCOAL ACNE CLEARING SCRUB cleans and exfoliates away acne-causing dirt and absorbs excess oil to help eliminate breakouts for clear skin.

- with Natural Charcoal

Drug Facts

Active ingredient

Salicylic acid 1%

Purpose

Acne treatment

Uses

- clears up acne blemishes
- penetrates pores to control acne blemishes
- helps prevent new acne blemishes from forming

Warnings

For external use only.

When using this product

- skin irritation and dryness is more likely to occur if you use another topical acne medication at the same time. If irritation occurs, only use one acne medication at a time.
- avoid contact with eyes. If contact occurs, rinse thoroughly with water.

Keep out of reach of children. If swallowed, get medical help or contact a Poison Control Center right away.

Directions

- wet face
- squeeze product into hands
- massage over entire face
- rinse thoroughly
- for optimal results, use up to 2-3 times per week

Other information

store at room temperature

Inactive ingredients

Water, Glycerin, Sodium Laureth Sulfate, Alumina, Cocamidopropyl Betaine, Sorbitol, Laureth-4 Carboxylic Acid, Synthetic Wax, Microcrystalline Wax, Ethylhexylglycerin, Acrylates/C10-30 Alkyl Acrylate Crosspolymer, Xanthan Gum, Fragrance, Sodium Hdroxide, Menthol, Polyquaternium-39, Charcoal Powder, Disodium EDTA, Talc, Sodium Benzoate,Red 30, Yellow 5 lake

Questions? 1-888-BIORE-11

www.biore.com @bioreus

BIORE is a trademark of Kao Corp.

Distributed by Kao USA Inc.

Cincinnati, OH 45214 ©2019

Made in USA of US & Imported Ingredients

PACKAGE LABEL

Biore

free your pores!

MEN'S SKINCARE

CHARCOAL ACNE CLEARING SCRUB

scrubs out acne-causing dirt & oil

SALICYLIC ACID ACNE TREATMENT

NET WT 4.5 OZ (127 g)